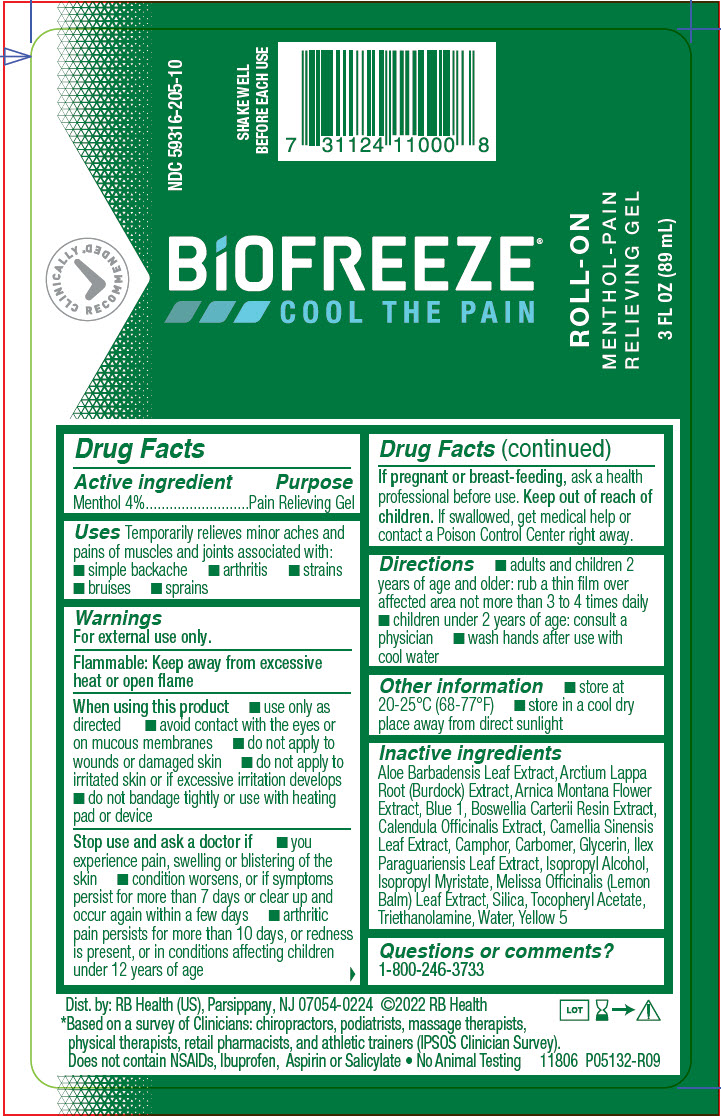 DRUG LABEL: Biofreeze Roll-On
NDC: 59316-205 | Form: GEL
Manufacturer: RB Health (US) LLC
Category: otc | Type: HUMAN OTC DRUG LABEL
Date: 20250703

ACTIVE INGREDIENTS: MENTHOL, UNSPECIFIED FORM 40 mg/1 mL
INACTIVE INGREDIENTS: ARNICA MONTANA FLOWER; FRANKINCENSE; CALENDULA OFFICINALIS FLOWER; ALOE VERA LEAF; GREEN TEA LEAF; GLYCERIN; ILEX PARAGUARIENSIS LEAF; ISOPROPYL ALCOHOL; ISOPROPYL MYRISTATE; MELISSA OFFICINALIS LEAF; SILICON DIOXIDE; .ALPHA.-TOCOPHEROL ACETATE; TROLAMINE; WATER; FD&C BLUE NO. 1; FD&C YELLOW NO. 5

Biofreeze®Roll-On

Drug Facts

Active ingredient

Menthol 4%

Purpose

Pain Relieving Gel

Uses

Temporarily relieves minor aches and pains of muscles and joints associated with:

- simple backache
- arthritis
- strains
- bruises
- sprains

Warnings

For external use only.

Flammable: Keep away from excessive heat or open flame

When using this product

- use only as directed
- avoid contact with the eyes or on mucous membranes
- do not apply to wounds or damaged skin
- do not apply to irritated skin or if excessive irritation develops
- do not bandage tightly or use with heating pad or device

Stop use and ask a doctor if

- you experience pain, swelling or blistering of the skin
- condition worsens, or if symptoms persist for more than 7 days or clear up and occur again within a few days
- arthritic pain persists for more than 10 days, or redness is present, or in conditions affecting children under 12 years of age

KEEP OUT OF REACH OF CHILDREN

If pregnant or breast-feeding,ask a health professional before use.

Keep out of reach of children.If swallowed, get medical help or contact a Poison Control Center right away.

Directions

- adults and children 2 years of age and older: rub a thin film over affected area not more than 3 to 4 times daily
- children under 2 years of age: consult a physician
- wash hands after use with cool water

Other information

- store at 20-25°C (68-77°F)
- store in a cool dry place away from direct sunlight

Inactive ingredients

Aloe Barbadensis Leaf Extract, Arctium Lappa Root (Burdock) Extract, Arnica Montana Flower Extract, Blue 1, Boswellia Carterii Resin Extract, Calendula Officinalis Extract, Camellia Sinensis Leaf Extract, Camphor, Carbomer, Glycerin, Ilex Paraguariensis Leaf Extract, Isopropyl Alcohol, Isopropyl Myristate, Melissa Officinalis (Lemon Balm) Leaf Extract, Silica, Tocopheryl Acetate, Triethanolamine, Water, Yellow 5

Questions or comments?

1-800-246-3733

Dist. by: RB Health (US), Parsippany, NJ 07054-0224

PRINCIPAL DISPLAY PANEL - 89 mL Bottle Carton

CLINICALLY
RECOMMENDED*

NDC 59316-205-10

BiOFREEZE®
COOL THE PAIN

ROLL-ON
MENTHOL-PAIN
RELIEVING GEL

3 FL OZ (89 mL)

SHAKE WELL
BEFORE EACH USE